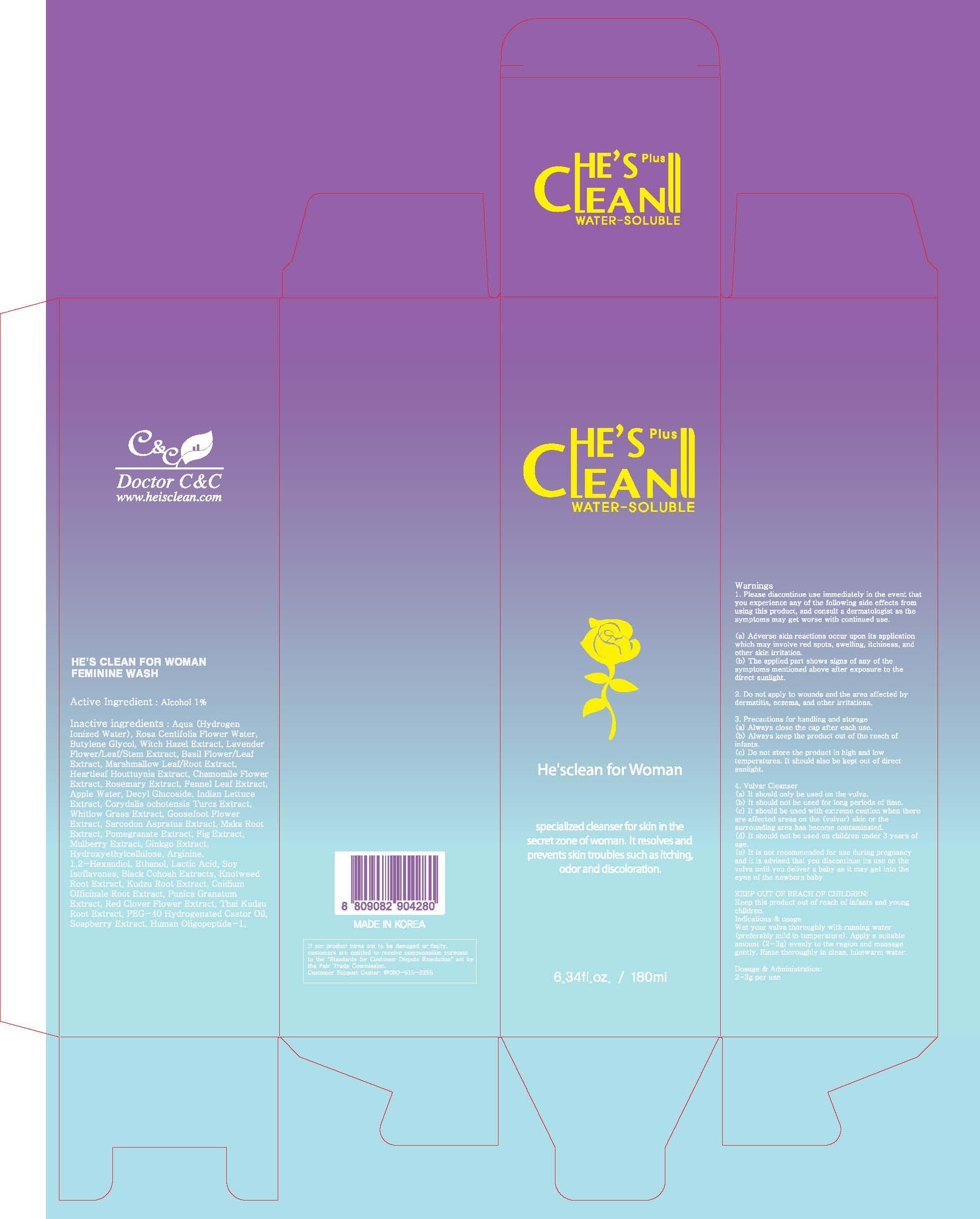 DRUG LABEL: HES CLEAN FOR WOMAN
NDC: 42979-140 | Form: SOLUTION
Manufacturer: DOCTOR C&C
Category: otc | Type: HUMAN OTC DRUG LABEL
Date: 20141203

ACTIVE INGREDIENTS: Alcohol 1.8 mg/180 mL
INACTIVE INGREDIENTS: WATER; Butylene Glycol

ACTIVE INGREDIENT

Active Ingredient: Alcohol 1%

INACTIVE INGREDIENT

Inactive ingredients: Aqua (Hydrogen Ionized Water), Rosa Centifolia Flower Water, Butylene Glycol, Witch Hazel Extract, Lavender Flower/Leaf/Stem Extract, Basil Flower/Leaf Extract, Marshmallow Leaf/Root Extract, Heartleaf Houttuynia Extract, Chamomile Flower Extract, Rosemary Extract, Fennel Leaf Extract, Apple Water, Decyl Glucoside, Indian Lettuce Extract, Corydalis ochotensis Turcz Extract, Whitlow Grass Extract, Goosefoot Flower Extract, Sarcodon Aspratus Extract, Maka Root Extract, Pomegranate Extract, Fig Extract, Mulberry Extract, Ginkgo Extract, Hydroxyethylcellulose, Arginine, 1,2-Hexandiol, Ethanol, Lactic Acid, Soy Isoflavones, Black Cohosh Extracts, Knotweed Root Extract, Kudzu Root Extract, Cnidium Officinale Root Extract, Punica Granatum Extract, Red Clover Flower Extract, Thai Kudzu Root Extract, PEG-40 Hydrogenated Castor Oil, Soapberry Extract, Human Oligopeptide-1, Ascorbic Acid, Pyridoxine HCl, Menthol, Damask Rose Oil

PURPOSE

Purpose: Antifungal

WARNINGS

1. Please discontinue use immediately in the event that you experience any of the following side effects from using this product, and consult a dermatologist as the symptoms may get worse with continued use.

(a) Adverse skin reactions occur upon its application which may involve red spots, swelling, itchiness, and other skin irritation.
(b) The applied part shows signs of any of the symptoms mentioned above after exposure to the direct sunlight.

2. Do not apply to wounds and the area affected by dermatitis, eczema, and other irritations.

3. Precautions for handling and storage
(a) Always close the cap after each use.
(b) Always keep the product out of the reach of infants.
(c) Do not store the product in high and low temperatures. It should also be kept out of direct sunlight.

4. Vulvar Cleanser
(a) It should only be used on the vulva.
(b) It should not be used for long periods of time.
(c) It should be used with extreme caution when there are affected areas on the (vulvar) skin or the surrounding area has become contaminated.
(d) It should not be used on children under 3 years of age.
(e) It is not recommended for use during pregnancy and it is advised that you discontinue its use on the vulva until you deliver a baby as it may get into the eyes of the newborn baby.

KEEP OUT OF REACH OF CHILDREN

Keep this product out of reach of infants and young children.

INDICATIONS & USAGE

Wet your vulva thoroughly with running water (preferably mild in temperature). Apply a suitable amount (2-3g) evenly to the region and massage gently. Rinse thoroughly in clean, lukewarm water.

DOSAGE & ADMINISTRATION

Dosage & Administration: 2-3g per use